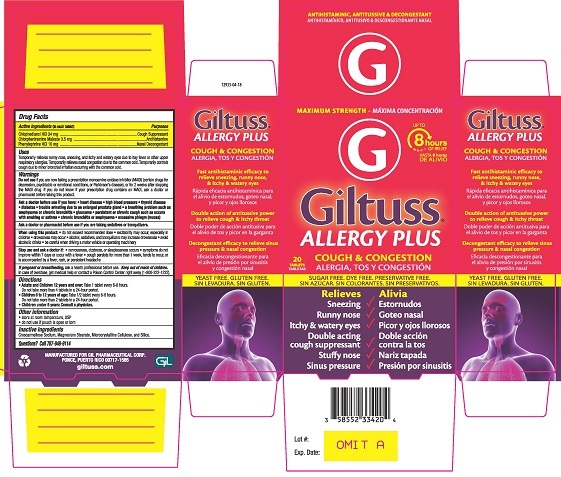 DRUG LABEL: Giltuss Allergy Plus
NDC: 58552-334 | Form: TABLET
Manufacturer: Gil Pharmaceutical Corp
Category: otc | Type: HUMAN OTC DRUG LABEL
Date: 20251009

ACTIVE INGREDIENTS: PHENYLEPHRINE HYDROCHLORIDE 10 mg/1 1; CHLORPHENIRAMINE MALEATE 3.5 mg/1 1; CHLOPHEDIANOL HYDROCHLORIDE 24 mg/1 1
INACTIVE INGREDIENTS: SILICON DIOXIDE; MICROCRYSTALLINE CELLULOSE; MAGNESIUM STEARATE; CROSCARMELLOSE SODIUM

Drug Facts

Active Ingredients (in each tablet)

Chlophedianol HCl 24 mg

Chlorpheniramine Maleate 3.5 mg

Phenylephrine HCl 10 mg

Purposes

Cough Suppressant

Antihistamine

Nasal Decongestant

Uses

Temporarily relieves runny nose, sneezing, and itchy and watery eyes due to hay fever or other upper respiratory allergies. Temporarily relieves nasal congestion due to the common cold. Temporarily controls cough due to minor bronchial irritation occurring with the common cold.

Warnings

DO NOT USE

Do not useif you are now taking a prescription monoamine oxidase inhibitor (MAOI) (certain drugs for depression, psychiatric or emotional conditions or Parkinson’s disease), or for 2 weeks after stopping the MAOI drug. If you do not know if your prescription drug contains an MAOI, ask a doctor or pharmacist before taking this product.

Ask a doctor before use if you have:

- heart disease
- high blood pressure
- thyroid disease
- diabetes
- trouble urinating due to an enlarged prostate gland
- a breathing problem such as emphysema or chronic bronchitis
- glaucoma
- persistent or chronic cough such as occurs with smoking, asthma
- chronic bronchitis, or emphysema
- excessive phlegm (mucus)

Ask a doctor or pharmacist before use if you are taking sedatives or tranquilizers.

When using this product:

- do not exceed recommended dose
- excitability may occur, especially in children
- drowsiness may occur
- alcohol, sedatives, and tranquilizers may increase drowsiness
- avoid alcoholic drinks
- be careful when driving a motor vehicle or operating machinery

Stop use and ask a doctor if:

- nervousness, dizziness, or sleeplessness occurs
- symptoms do not improve within 7 days or occur with a fever
- cough persists for more than 1 week, tends to recur, or is accompanied by a fever, rash or persistent headache

PREGNANCY OR BREAST FEEDING

If pregnant or breast-feeding, ask a health professional before use

Keep out of reach of children.In case of overdose, get medical help or contact a Poison Control Center right away (1-800-222-1222).

Directions

- Adults and Children 12 years and over:Take 1 tablet every 6-8 hours. Do not take more than 4 tablets in a 24-hour period.
- Children 6 to 12 years of age:Take 1/2 tablet every 6-8 hours. Do not take more than 2 tablets in a 24-hour period.
- Children under 6 years: Consult a physician.

Other information

- store at room temperature, USP
- do not use if pouch is open or torn

Inactive Ingredients

Croscarmellose Sodium, Magnesium Stearate, Microcrystalline Cellulose and Silica.

Questions? Call 787-848-9114

PACKAGE LABEL

MAXIMUM STRENGTH

Giltuss® ALLERGY PLUS

COUGH & CONGESTION

20 TABLETS

SUGAR FREE. DYE FREE. PRESERVATIVE FREE.

Relieves

- Sneezing
- Runny Nose
- Itchy & watery eyes
- Double acting cough supressant
- Stuffy Nose
- Sinus Pressure